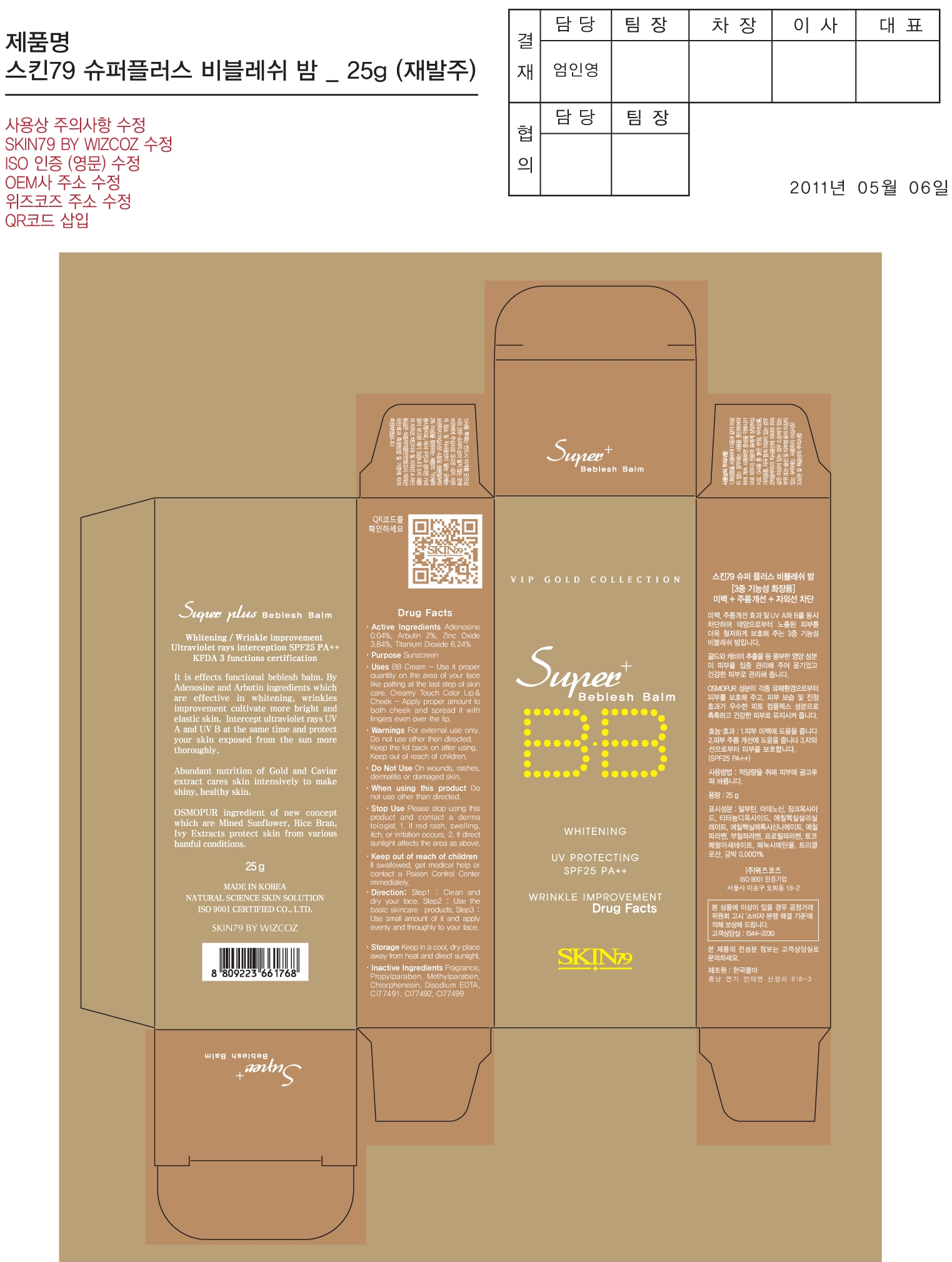 DRUG LABEL: SuperPlus Beblesh Balm SPF25 PA 2Plus
NDC: 49715-017 | Form: CREAM
Manufacturer: WIZCOZ CORPORATION LTD
Category: otc | Type: HUMAN OTC DRUG LABEL
Date: 20120201

ACTIVE INGREDIENTS: TITANIUM DIOXIDE 1.56 g/25 g; ZINC OXIDE 0.96 g/25 g; ARBUTIN 0.5 g/25 g; ADENOSINE 0.01 g/25 g
INACTIVE INGREDIENTS: CHLORPHENESIN; EDETATE DISODIUM; METHYLPARABEN; PROPYLPARABEN

Purpose: Sunscreen

ACTIVE INGREDIENT

Active Ingredients: Titanium Dioxide 6.24%, Zinc Oxide 3.84%, Arbutin 2.00%, Adenosine 0.04%

When using this product: Do not use other than directed

Do Not Use: On wounds, rashes, dermatitis or damaged skin

Keep Out of Reach of Children: If swallowed, get medical help or contact a Poison Control Center immediately

Stop Use: Please stop using this product and contact a dermatologist.
1. If red rash, swelling, itch or irritation occurs
2. If direct sunlight affects the area as above

WARNINGS

Warnings: For external use only. Do not use other than directed. Keep the lid back on after using

STORAGE AND HANDLING

Storage: Keep in a cool, dry place away from heat and direct sunlight

DESCRIPTION

Direction:
Step 1: Clean and dry your face
Step 2: Use the basic skincare products
Step 3: Use small amount of it and apply evenly and thoroughly to your face

INACTIVE INGREDIENT

Inactive Ingredients:Chlorphenesin, Disodium EDTA, Methylparaben, Propylparaben